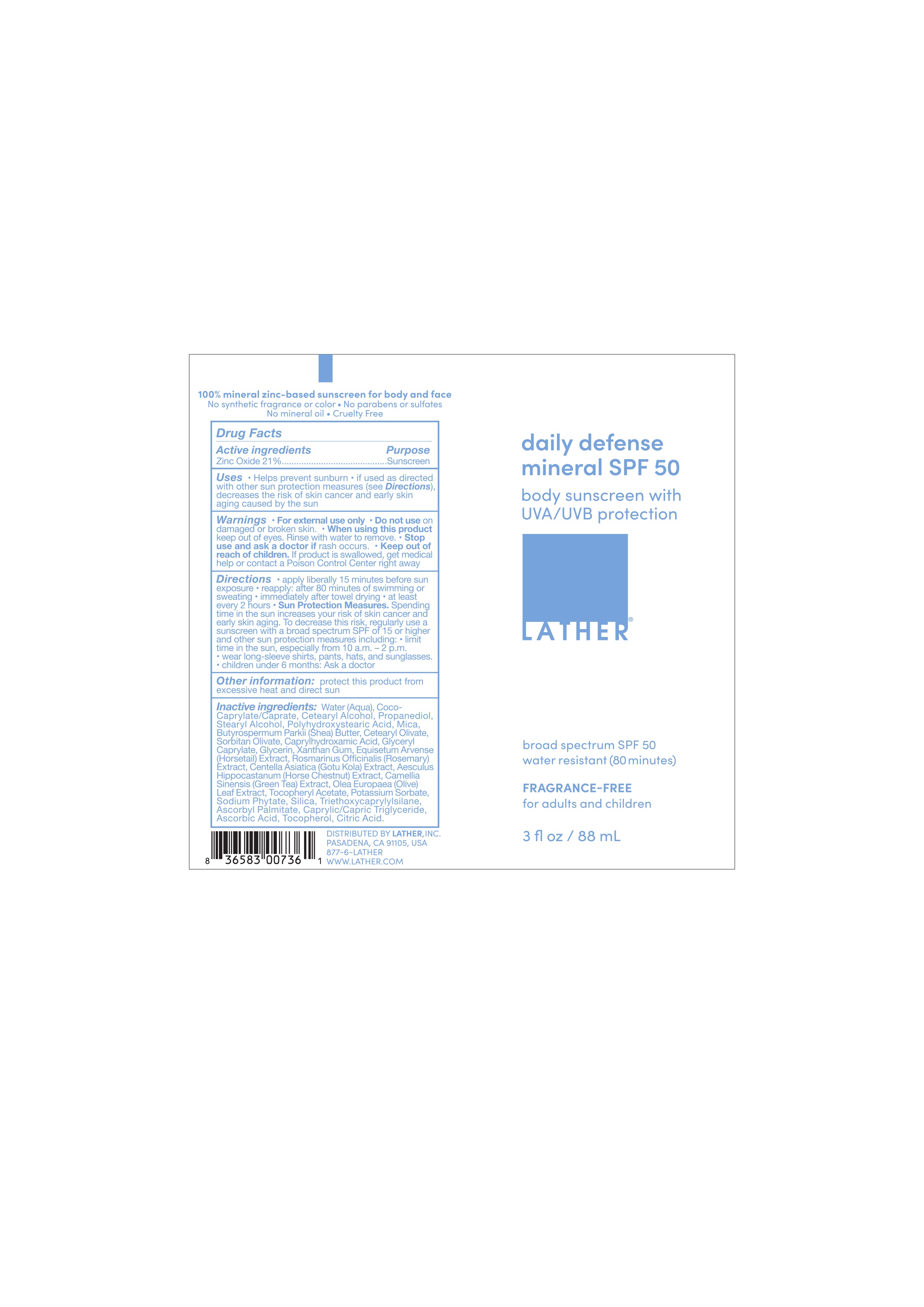 DRUG LABEL: LATHER- DAILY DEFENSE MINERAL SPF 50 BODY SUNSCREEN
NDC: 77394-203 | Form: CREAM
Manufacturer: Lather, Inc.
Category: otc | Type: HUMAN OTC DRUG LABEL
Date: 20251015

ACTIVE INGREDIENTS: ZINC OXIDE 21 g/100 mL
INACTIVE INGREDIENTS: WATER; STEARYL ALCOHOL; OLEA EUROPAEA (OLIVE) LEAF; POTASSIUM SORBATE; ASCORBIC ACID; MICA; CAPRYLHYDROXAMIC ACID; TOCOPHEROL; GLYCERIN; CETEARYL ALCOHOL; PROPANEDIOL; XANTHAN GUM; CENTELLA ASIATICA; GLYCERYL CAPRYLATE; POLYHYDROXYSTEARIC ACID (2300 MW); COCO-CAPRYLATE/CAPRATE; BUTYROSPERMUM PARKII (SHEA) BUTTER; SILICA; CITRIC ACID; TRIETHOXYCAPRYLYLSILANE; SODIUM PHYTATE; ALPHA-TOCOPHEROL ACETATE; ASCORBYL PALMITATE; CAPRYLIC/CAPRIC TRIGLYCERIDE; EQUISETUM ARVENSE BRANCH; SORBITAN OLIVATE; CETEARYL OLIVATE; HORSE CHESTNUT

LATHER- DAILY DEFENSE MINERAL SPF 50 BODY SUNSCREEN

Active Ingredients

Zinc Oxide 21%

Purpose Sunscreen

Uses

• Helps prevent sunburn

• if used as directed with other sun protection measures (see Directions), decreases the risk of skin cancer and early skin aging caused by the sun

Warnings For external use only

Do not use on damaged or broken skin

When using this product keep out of eyes. Rinse with water to remove.

Stop use and ask a doctor if rash occurs

Keep out of reach of children. If product is swallowed, get medical help or contact a Poison Control Center right away.

Other information: protect this product from excessive heat and direct

DOSAGE AND ADMINISTRATION

Directions: Apply liberally 15 minutes before sun exposure. reapply: after 80 minutes of swimming or sweating. immediately after towel drying. at least every 2 hours. Sun Protection Measures. Spending time in the sun increases your risk of skin cancer and early skin aging. To decrease this risk, regularly use a sunscreen with a Broad Spectrum SPF of 15 or higher and other sun protection measures including: limit time in the sun, especially from 10 a.m. - 2 p.m., wear long-sleeve shirts, pants, hats, and sunglasses, children under 6 months of age: ask a doctor

INACTIVE INGREDIENT

Inactive ingredients: Water (Aqua), Coco Caprylate/Caprate, Cetearyl Alcohol, Propanediol, Stearyl Alcohol, Polyhydroxystearic Acid, Mica, Butyrospermum Parkii (Shea) Butter, Cetearyl Olivate, Sorbitan Olivate, Caprylhydroxamic Acid, Glyceryl Caprylate, Glycerin, Xanthan Gum, Equisetum Arvense (Horsetail) Extract, Rosmarinus Officinalis (Rosemary) Extract, Centella Asiatica (Gotu Kola) Extract, Aesculus Hippocastanum (Horse Chestnut) Extract, Camellia Sinensis (Green Tea) Extract, Olea Europaea (Olive) Leaf Extract, Tocopheryl Acetate, Potassium Sorbate, Sodium Phytate, Silica, Triethoxycaprylylsilane, Ascorbyl Palmitate, Caprylic/Capric Triglyceride, Ascorbic Acid, Tocopherol, Citric Acid

Lather - daily defense mineral SPF 50 - 3 fl oz / 88 mL

daily defense mineral SPF 50
body sunscreen with UVA/UVB protection

Lather

broad spectrum SPF 50

water resistant (80 minutes)

FRAGRANCE-FREE

for adults and children

3 fl oz / 88 mL